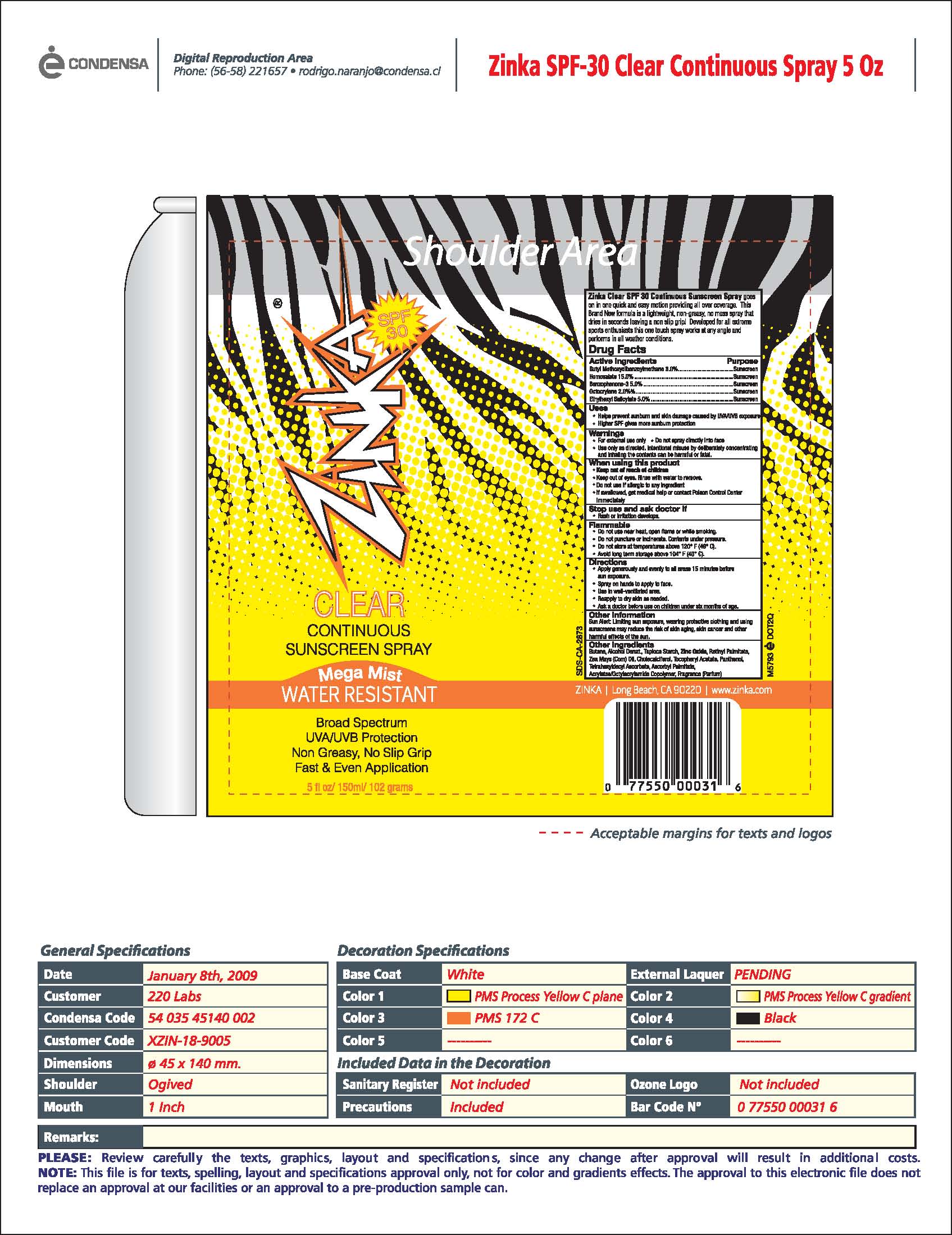 DRUG LABEL: SUNSCREEN
NDC: 57367-029 | Form: AEROSOL, SPRAY
Manufacturer: 220 Laboratories Inc
Category: otc | Type: HUMAN OTC DRUG LABEL
Date: 20100517

ACTIVE INGREDIENTS: HOMOSALATE 150 mg/1 g; OXYBENZONE 50 mg/1 g; OCTISALATE 50 mg/1 g; AVOBENZONE 30 mg/1 g; OCTOCRYLENE 20 mg/1 g
INACTIVE INGREDIENTS: STARCH, TAPIOCA; ZINC OXIDE; COUMARIN; BENZYL SALICYLATE; PANTHENOL; BENZYL BENZOATE; ASCORBYL PALMITATE; TETRAHEXYLDECYL ASCORBATE; VITAMIN A PALMITATE; CORN OIL; CHOLECALCIFEROL; .ALPHA.-TOCOPHEROL ACETATE, DL-

SPF-30 Artwork

Active Ingredients Purpose

Butyl Methoxydibenzoylmethane 3.0%................................Sunscreen

Homosalate 15.0%............................................................Sunscreen

Benzophenone-3 5.0%.......................................................Sunscreen

Octocrylene 2.0%..............................................................Sunscreen

Ethylhexyl Salicylate 5.0%.................................................Sunscreen

When Using this product

- Keep out of reach of children
- Keep out of eyes. Rinse with water to remove.
- Do not use if allergic to any ingredient.
- If swallowed, get medical help or contact Poison Control Center immediately.

Warnings

- For external use only
- Do not spray directly into face
- Use only as directed. Intentional misuse by deliberately concentrating and inhaling the contents can be harmful or fatal.

Stop use and ask doctor if

- Rash or irritation develops.

STORAGE AND HANDLING

Flammable

- Do not use near heat, open flame or while smoking.
- Do not puncture or incinerate. Contents under pressure.
- Do not store at temperature about 120°F (49°C).
- Avoid long term storage about 104°F (40°C).

Directions

- Apply generously and evenly to all areas 15 minutes before sun exposure.
- Spray on hands and apply to face.
- Use in well-ventilated area.
- Reapply to dry skin as needed.
- Ask doctor before use on children under six months of age.

Other Information

Sun Alert: Limiting sun exposure, wearing protective clothing and using sunscreens may reduce the risk of skin aging, skin cancer and other harmful effects of the sun.

INACTIVE INGREDIENT

Other Ingredients

Butane, Alcohol Denat., Taploca Starch, Zinc Oxide, Retinyl Palmitate, Zea Mays (Corn) oil, Cholecalciferol, Tocopheryl Acetate, Panthenol, Tetrahexyldecyl Ascorbate, Ascorbyl Palmitate, Acrylates/Octylacylamide Copolymer, Fragrance (Parfum)

Active Ingredients Purpose

Butyl Methoxydibenzoylmethane 3.0%................................Sunscreen

Homosalate 15.0%............................................................Sunscreen

Benzophenone-3 5.0%.......................................................Sunscreen

Octocrylene 2.0%..............................................................Sunscreen

Ethylhexyl Salicylate 5.0%.................................................Sunscreen

PACKAGE LABEL

Zinka Clear continuous sunscreen spray
Mega mist water resistant
Broad spectrum
UVA/UVB Protection
Non-greasy, no slip grip
Fast and even application